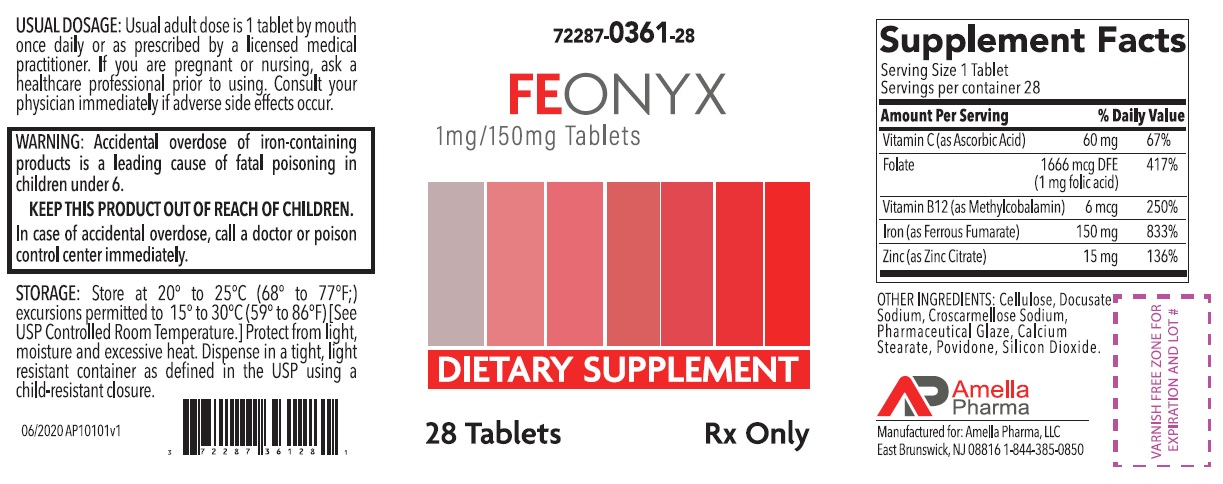 DRUG LABEL: FEONYX
NDC: 72287-361 | Form: TABLET, COATED
Manufacturer: Amella Pharma, LLC
Category: other | Type: DIETARY SUPPLEMENT
Date: 20201120

ACTIVE INGREDIENTS: ASCORBIC ACID 60 mg/1 1; FOLIC ACID 1 mg/1 1; METHYLCOBALAMIN 6 ug/1 1; FERROUS FUMARATE 150 mg/1 1; ZINC CITRATE 15 mg/1 1
INACTIVE INGREDIENTS: POWDERED CELLULOSE; DOCUSATE SODIUM; CROSCARMELLOSE SODIUM; SHELLAC; CALCIUM STEARATE; POVIDONE, UNSPECIFIED; SILICON DIOXIDE

FEONYX
Tablets with 150 mg Ferrous Fumarate

HEALTH CLAIM: FEONYX Tablets Dietary Supplement with Iron Dispensed by Prescription†

Supplements Facts
Serving Size: 1 Tablet
Servings per container: 28
 | Amount per; Serving | % Daily; Value
Vitamin C (as Ascorbic Acid) | 60 mg | 67%
Folate (1 mg Folic Acid) | 1666 mcg DFE | 417%
Vitamin B12 (as Methylcobalamin) | 6 mcg | 250%
Iron (as Ferrous Fumarate); (Equivalent to about 50mg of Elemental Iron) | 150 mg | 833%
Zinc (as Zinc Citrate) | 15 mg | 136%

OTHER INGREDIENTS: Cellulose, Docusate Sodium, Croscarmellose Sodium, Pharmaceutical Glaze, Calcium Stearate, Povidone, Silicon Dioxide

DESCRIPTION

FEONYX Tablets is a professionally prescribed orally administrated hematinic multivitamin/multimineral dietary supplement used to improve the nutritional status of patients with iron deficiency; this includes women prior to conception, throughout pregnancy, and in the postnatal period for both lactating and non-lactating mothers. THIS PRODUCT IS NOT INDICATED FOR USE IN CHILDREN.

FEONYX Tablets are small, round, dark brown, clear-coated tablet, with debossed "A" on one side.

CONTRAINDICATIONS

FEONYX should not be used by patients with a known hypersensitivity to any of the listed ingredients. All iron compounds are contraindicated in patients with hemochromatosis, hemosiderosis, or hemolytic anemias.

PRECAUTIONS:

General: Take 2 hours after meals. Do not exceed recommended dose. Discontinue use if symptoms of intolerance appear. The type of anemia and the underlying cause or causes should be determined before starting therapy with FEONYX tablets. Ensure Hgb, Hct, Reticulocyte count are determined before starting therapy and periodically thereafter during prolonged treatment. Periodically review therapy to determine if it needs to be continued without change or if a dose change is indicated. Since the anemia may be a result of a systemic disturbance, such as recurrent blood loss, the underlying cause or causes should be corrected, if possible.

Folic Acid: Folic acid alone is an improper therapy in the treatment of pernicious anemia and other megaloblastic anemias where vitamin B12 is deficient. Folic acid in doses above 0.1 mg daily may obscure pernicious anemia assessment, such that hematologic remission can occur while neurological manifestations remain progressive. Allergic sensitization has been reported following both oral and parenteral administration of folic acid.

The patient’s medical conditions and consumption of other drugs, herbs, and/or supplements should be considered.

Pediatric Use: Safety and effectiveness in pediatric population have not been established.

Geriatric Use: Safety and effectiveness in elderly population have not been established.

KEEP OUT OF REACH OF CHILDREN.

DRUG INTERACTIONS

Prescriber should be aware of a number of iron/drug interactions, including antacids, tetracyclines, or fluoroquinolones

ADVERSE REACTIONS

Adverse reactions with iron therapy may include GI irritation, constipation, diarrhea, nausea, vomiting, and dark stools. Adverse reactions with iron therapy are usually transient. Allergic sensitization has been reported following both oral and parental administration of folic acid.

OVERDOSAGE

The clinical course of acute iron overdosage can be variable. Symptoms may include abdominal pain, metabolic acidosis, anuria, CNS damage, coma, convulsions, death, dehydration, diffuse vascular congestion, hepatic cirrhosis, hypotension, hypothermia, lethargy, nausea, vomiting, diarrhea, tarry stools, melena, hematemesis, hypotension, tachycardia, hyperglycemia, dehydration, drowsiness, pallor, cyanosis, lassitude, seizures, and shock.

WARNINGS

Folic acid alone is improper therapy in the treatment of pernicious anemia and other megaloblastic anemias where vitamin B12 is deficient.

WARNING: Accidental overdose of iron-containing products is a leading cause of fatal poisoning in children under 6. KEEP THIS PRODUCT OUT OF REACH OF CHILDREN. In case of accidental overdose, call a doctor or poison control center immediately.

DOSAGE AND ADMINISTRATION

Usual adult dose is 1 tablet by mouth once daily or as directed by a physician. Do not chew tablet.

HOW SUPPLIED

FEONYX Tablets are small, round, dark brown, clear-coated tablet, with debossed "A" on one side.

FEONYX Tablets is available as the following:
72287-361-28* 28ct bottle

STORAGE

Store at 20° to 25°C (68° to 77°F); excursions permitted to 15° to 30°C (59° to 86°F) [See USP Controlled Room Temperature]. Protect from light, moisture and avoid excessive heat. Dispense in a tight, light resistant container as defined by the USP using a child-resistant closure.

Manufactured for:
Amella Pharma, LLC
E Brunswick, NJ 08816

Call your doctor for medical advice about side effects. You may report side effects to Amella Pharma, LLC at 1-844-385-0850.

Issued: 06/2020 AP10102v1

*Amella Pharma does not represent these product codes to be National Drug Codes (NDC). Product codes are formatted according to standard industry practice, to meet the formatting requirement by pedigree reporting and supply-chain control including pharmacies.

† This product is a prescription-folate with or without other dietary ingredients that – due to increased folate levels increased risk associated with masking of B12 deficiency (pernicious anemia) requires administration under the care of a licensed medical practitioner (61 FR 8760). The most appropriate way to ensure pedigree reporting consistent with these regulatory guidelines and safety monitoring is to dispense this product only by prescription (Rx). This is not an Orange Book product. This product may be administered only under a physician’s supervision and all prescriptions using this product shall be pursuant to state statutes as applicable. The ingredients, indication or claims of this product are not to be construed to be drug claims.
1. Federal Register Notice of August 2, 1973 (38 FR 20750)
2. Federal Register Notice of October 17, 1980 (45 FR 69043, 69044)
3. Federal Register Notice of March 5, 1996 (61 FR 8760)